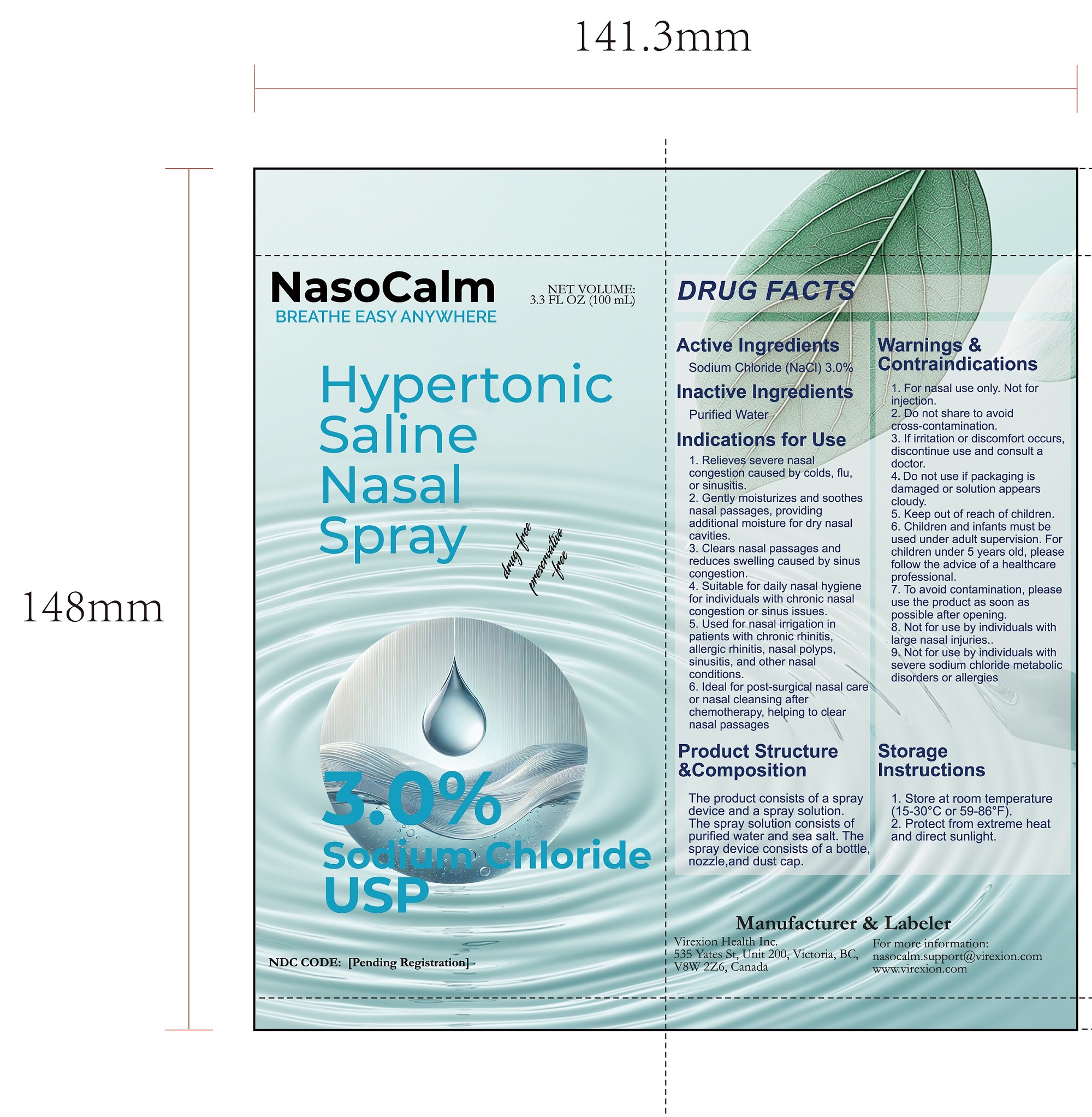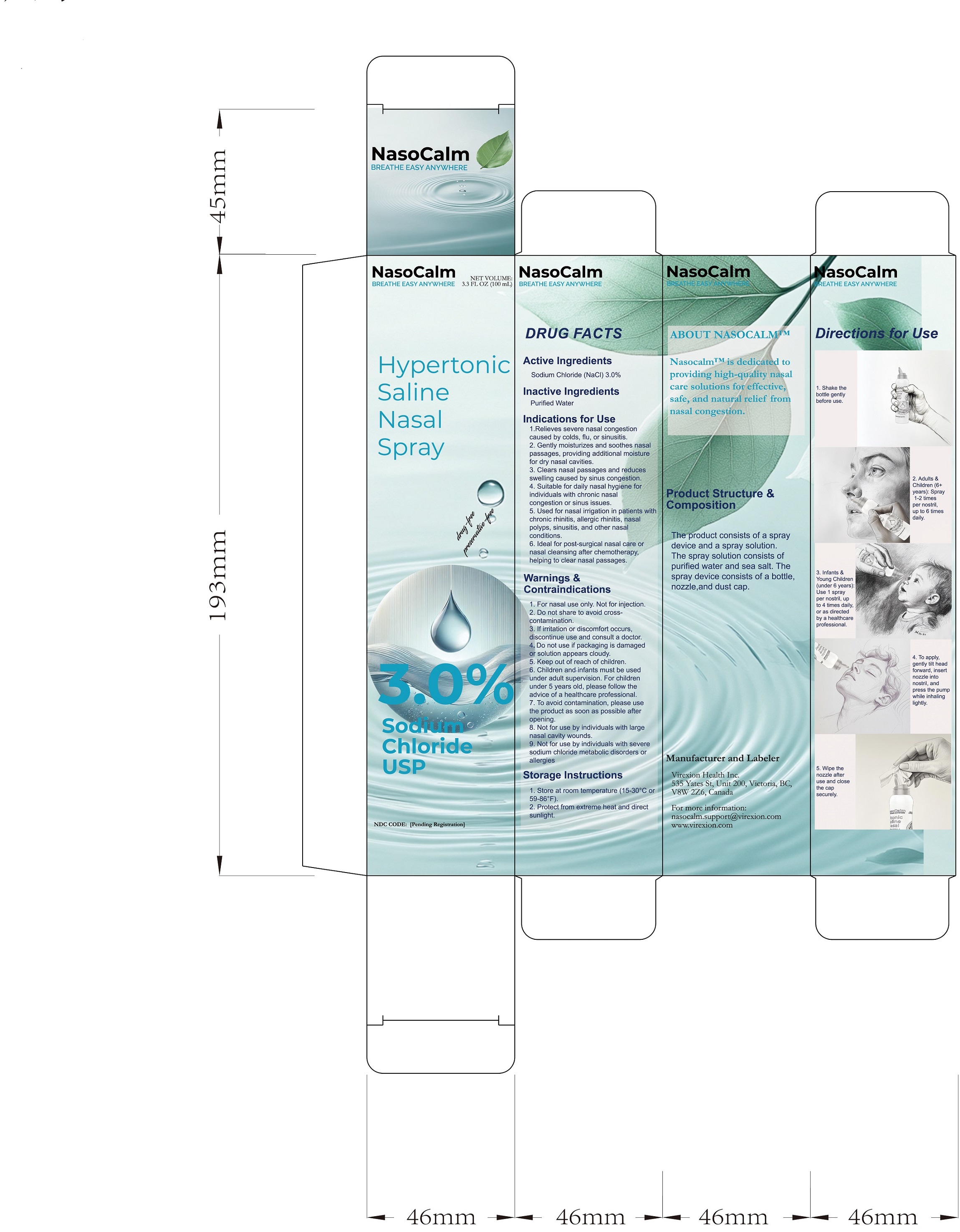 DRUG LABEL: Nasocalm
NDC: 85436-003 | Form: SPRAY
Manufacturer: Virexion Health Inc.
Category: otc | Type: HUMAN OTC DRUG LABEL
Date: 20250328

ACTIVE INGREDIENTS: SODIUM CHLORIDE 3 mg/100 mg
INACTIVE INGREDIENTS: WATER

ACTIVE INGREDIENT

Sodium Chloride (NaCl) 3.0%

PURPOSE

Reduces nasal congestion, clears mucus and allergens, and assists in relieving symptoms of chronic nasal congestion or sinusitis by drawing out excess fluid from swollen nasal tissues.

INDICATIONS AND USAGE

Relieves severe nasal congestion caused by colds, flu, or sinusitis.
Gently moisturizes and soothes nasal passages, providing additional moisture for dry nasal cavities.
Clears nasal passages and reduces swelling caused by sinus congestion.
Suitable for daily nasal hygiene for individuals with chronic nasal congestion or sinus issues.
Used for nasal irrigation in patients with chronic rhinitis, allergic rhinitis, nasal polyps, sinusitis, and other nasal conditions.
Ideal for post-surgical nasal care or nasal cleansing after chemotherapy, helping to clear nasal passages.

WARNINGS

For nasal use only. Not for injections.

Do not share to avoid cross-contamination.
To avoid contamination, please use the product as soon as possible after opening

Do not use if packaging is damaged or solution appears cloudy.
Not for use by individuals with large nasal cavity wounds.
Not for use by individuals with severe sodium chloride metabolic disorders or allergies.

STOP USE

If irritation or discomfort occurs, stop use and consult a doctor

Keep out of reach of children.

Directions

1. Shake the bottle gently before use.

2. Adults & Children (6+ years): Spray 1-2 times per nostril, up to 6 times daily.

3. Infants & Young Children (under 6 years): Use 1 spray per nostril, up to 4 times daily, or as directed by a healthcare professional.

4. To apply, gently tilt head forward, insert nozzle into nostril, and press the pump while inhaling lightly.

5. Wipe the nozzle after use and close the cap securely.

6. Children and infants must be used under adult supervision. For children under 5 years old, please follow the advice of a healthcare professional.

STORAGE AND HANDLING

1. Store at room temperature (15-30°C or 59-86°F).

2. Protect from extreme heat and direct sunlight.

INACTIVE INGREDIENT

Purified water USP